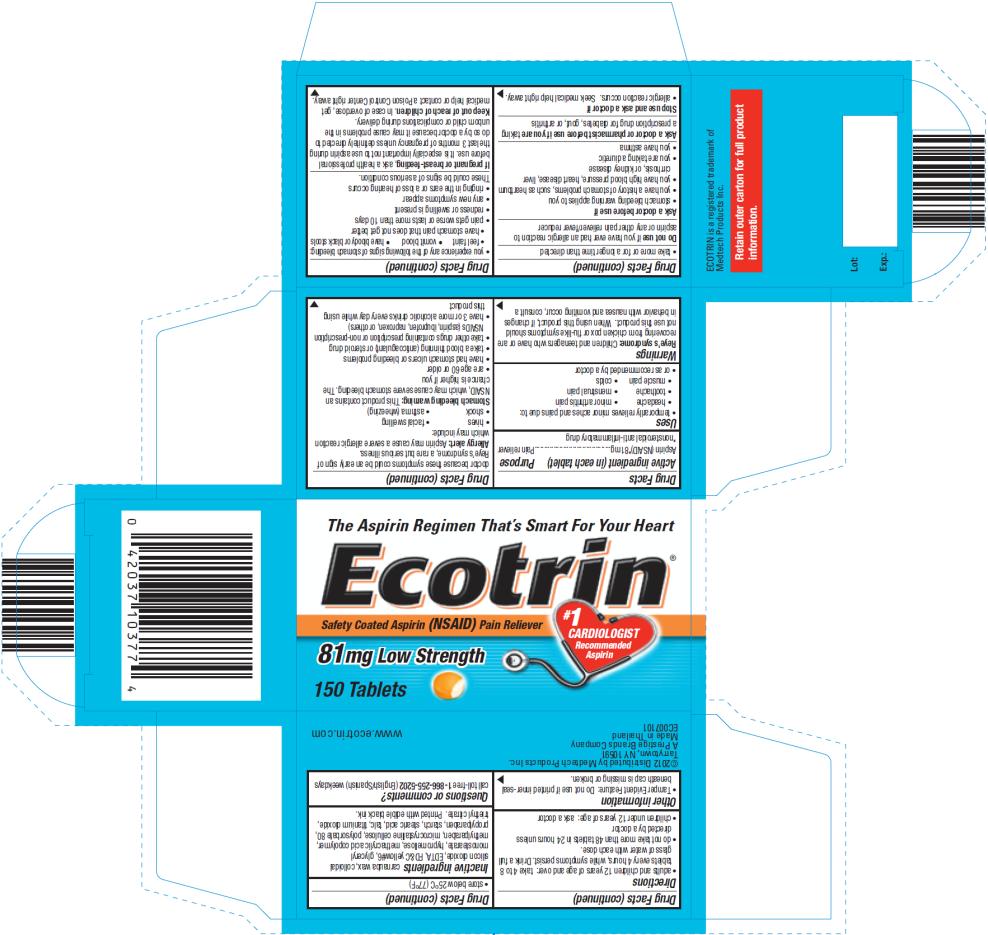 DRUG LABEL: Ecotrin
NDC: 63029-301 | Form: TABLET, COATED
Manufacturer: Medtech Products Inc.
Category: otc | Type: HUMAN OTC DRUG LABEL
Date: 20120716

ACTIVE INGREDIENTS: ASPIRIN 81 mg/1 1
INACTIVE INGREDIENTS: CARNAUBA WAX; SILICON DIOXIDE; EDETIC ACID; FD&C YELLOW NO. 6; GLYCERYL MONOSTEARATE; HYPROMELLOSES; METHYLPARABEN; METHACRYLIC ACID - ETHYL ACRYLATE COPOLYMER (1:1) TYPE A; CELLULOSE, MICROCRYSTALLINE; POLYSORBATE 80; STARCH, CORN; PROPYLPARABEN; STEARIC ACID; TALC; TITANIUM DIOXIDE; TRIETHYL CITRATE

Ecotrin Low Strength

Drug Facts

Active ingredient

(in each tablet)

Aspirin (NSAID) *81mg

*nonsteroidal anti-inflammatory drug

Purpose

Pain reliever

Uses

- temporarily relieves minor aches and pains due to:
  - headache
  - minor arthritis pain
  - toothache
  - menstrual pain
  - colds
- or as recommended by a doctor

Warnings

Reye’s syndrome: Children and teenagers who have or are recovering from chicken pox or flu-like symptoms should not use this product. When using this product, if changes in behavior with nausea and vomiting occur, consult a doctor because these symptoms could be an early sign of Reye’s syndrome, a rare but serious illness.

Allergy alert: Aspirin may cause a severe allergic reaction which may include:

- hives
- shock
- facial swelling
- asthma (wheezing)

Stomach bleeding warning: This product contains an NSAID, which may cause severe stomach bleeding. The chance is higher if you

- are age 60 or older
- have had stomach ulcers or bleeding problems
- take a blood thinning (anticoagulant) or steroid drug
- take other drugs containing prescription or nonprescription NSAIDs (aspirin, ibuprofen, naproxen, or others)
- have 3 or more alcoholic drinks every day while using this product
- take more or for a longer time than directed

Do not use

if you have ever had an allergic reaction to aspirin or any other pain reliever/fever reducer

Ask a doctor before use if

- stomach bleeding warning applies to you
- you have a history of stomach problems, such as heartburn
- you have high blood pressure, heart disease, liver cirrhosis, or kidney disease
- you are taking a diuretic
- you have asthma

Ask a doctor or pharmacist before use if you are

taking a prescription drug for diabetes, gout, or arthritis

Stop use and ask a doctor if

- allergic reaction occurs. Seek medical help right away.
- you experience any of the following signs of stomach bleeding:
  - feel faint
  - vomit blood
  - have bloody or black stools
  - have stomach pain that does not get better
- pain gets worse or lasts more than 10 days
- redness or swelling is present
- any new symptoms appear
- ringing in the ears or a loss of hearing occurs

These could be signs of a serious condition.

If pregnant or breast-feeding,

ask a health professional before use. It is especially important not to use aspirin during the last 3 months of pregnancy unless definitely directed to do so by a doctor because it may cause problems in the unborn child or complications during delivery.

Keep out of reach of children.

In case of overdose, get medical help or contact a Poison Control Center right away.

Directions

- adults and children 12 years of age and over: take 4 to 8 tablets every 4 hours, while symptoms persist. Drink a full glass of water with each dose.
- do not take more than 48 tablets in 24 hours unless directed by a doctor
- children under 12 years of age: ask a doctor

Other information

- Tamper Evident Feature: Do not use if printed inner-seal beneath cap is missing or broken.
- store below 25ºC (77ºF)

Inactive ingredients

carnauba wax, colloidal silicon dioxide, EDTA, FD&C yellow#6, glyceryl monostearate, hypromellose, methacrylic acid copolymer, methylparaben, microcrystalline cellulose, polysorbate 80, propylparaben, starch, stearic acid, talc, titanium dioxide, triethyl citrate. Printed with edible ink.

Questions or comments?

call toll-free 1-866-255-5202 (English/Spanish) weekdays

PRINCIPAL DISPLAY PANEL

The Aspirin Regimen That’s Smart For Your Heart
Ecotrin®
Safety Coated Aspirin (NSAID) Pain Reliever
#1 CARDIOLOGIST Recommended Aspirin
81 mg Low Strength
150 Tablets